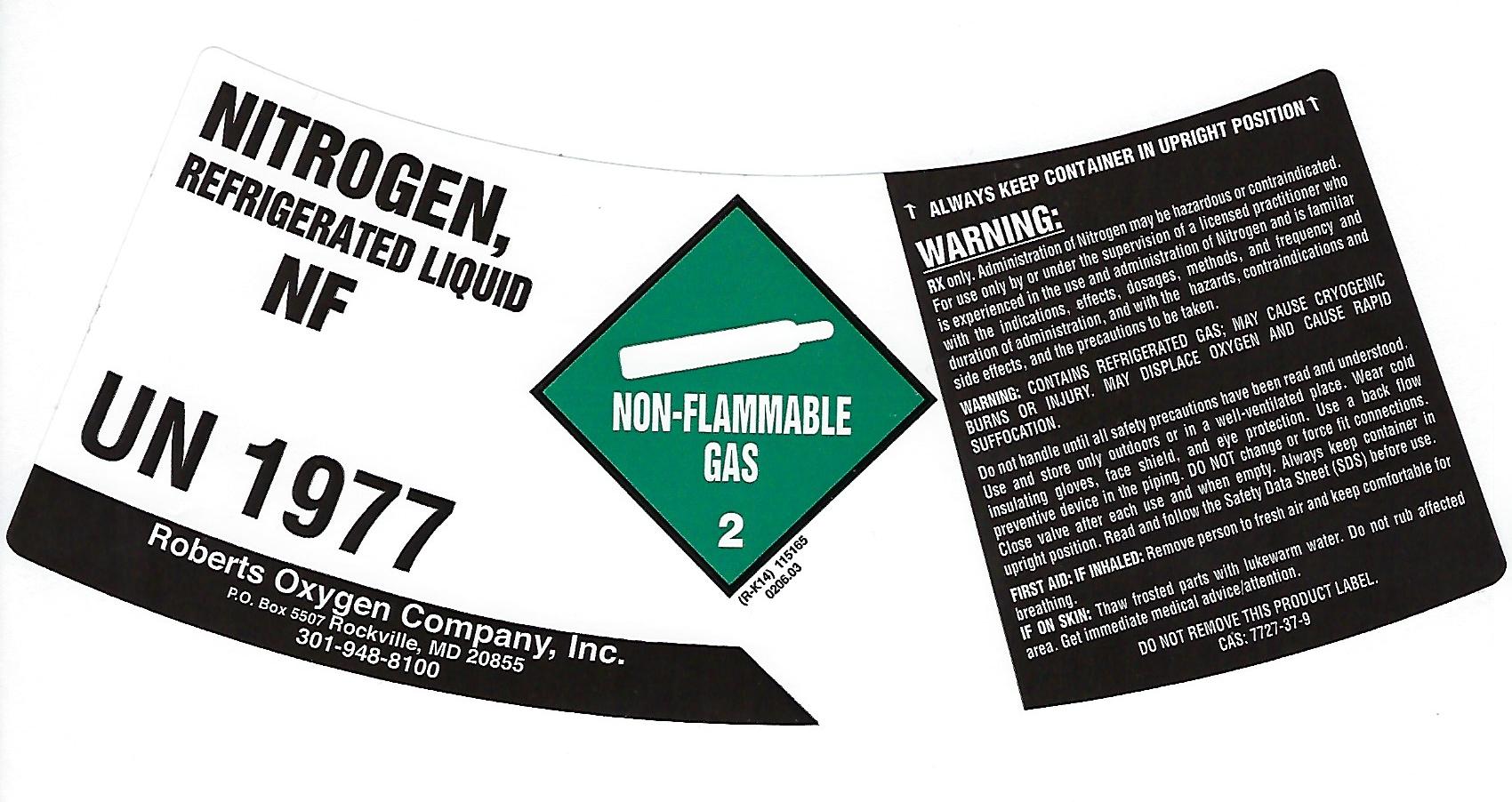 DRUG LABEL: Nitrogen
NDC: 46123-004 | Form: GAS
Manufacturer: Roberts Oxygen Company, Inc
Category: prescription | Type: HUMAN PRESCRIPTION DRUG LABEL
Date: 20251117

ACTIVE INGREDIENTS: NITROGEN 990 mL/1 L

Nitrogen-004

PACKAGE LABEL

NITROGEN,
REFRIGERATED LIQUID
NF
UN1977
Roberts Oxygen Company, Inc.
P.O. Box 5507 Rockville, MD 20855
301-948-8100
NON-FLAMMABLE GAS 2
↑ALWAYS KEEP CONTAINER IN UPRIGHT POSITION↑
WARNING:
Rx only. Administration of Nitrogen may be hazardous or contraindicated. For use only by or under the supervision of a licensed practitioner who is experienced in the use and administration of nitrogen and is familiar with the indications, effects, dosages, methods, and frequency and duration of administration, and the hazards, contraindications and side effects and the precautions to be taken.
WARNING: CONTAINS REFRIGERATED GAS; MAY CAUSE CRYOGENIC BURNS OR INJURY. MAY DISPLACE OXYGEN AND CAUSE RAPID SUFFOCATION.
Do not handle until all safety precautions have been read and understood. Use and store only outdoors or in a well-ventilated place. Wear cold insulating gloves, face shield, and eye protection. Use a back flow preventative device in the piping. DO NOT change or force fit connections. Close valve after each use and when empty. Always keep container in upright position. Read and follow the Safety Data Sheet (SDS) before use.
FIRST AID: IF INHALED: Remove person to fresh air and keep comfortable for breathing.
IF ON SKIN: Thaw frosted parts with lukewarm water. Do not rub affected area. Get immediate medical advice/attention.
DO NOT REMOVE THIS PRODUCT LABEL.
CAS: 7727-37-9